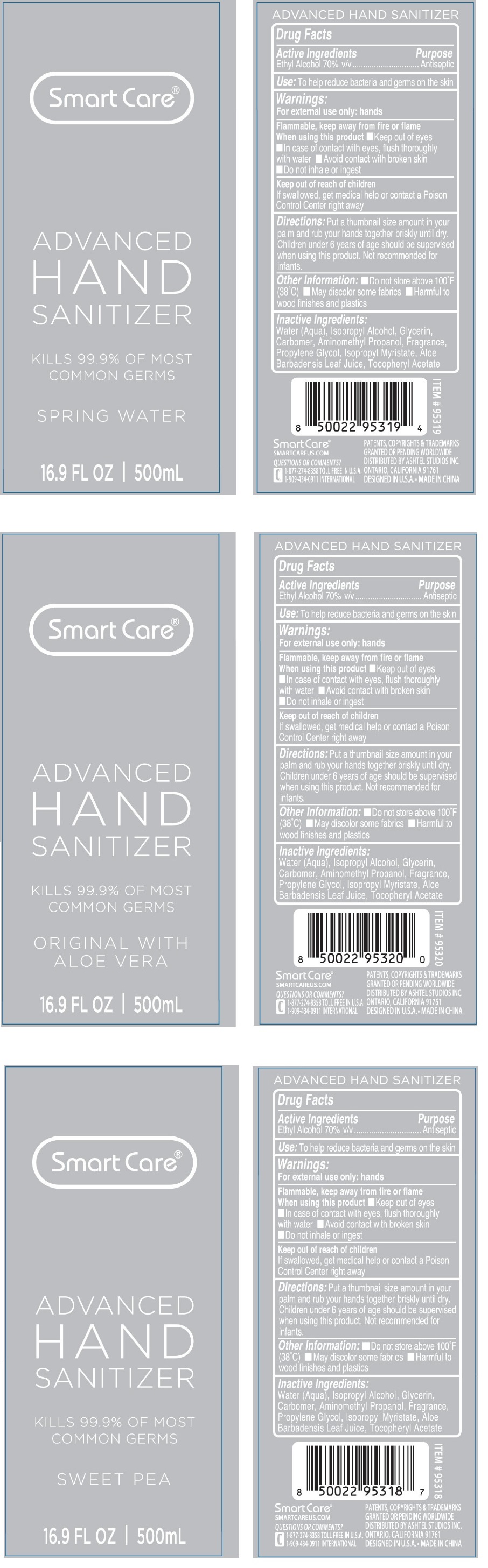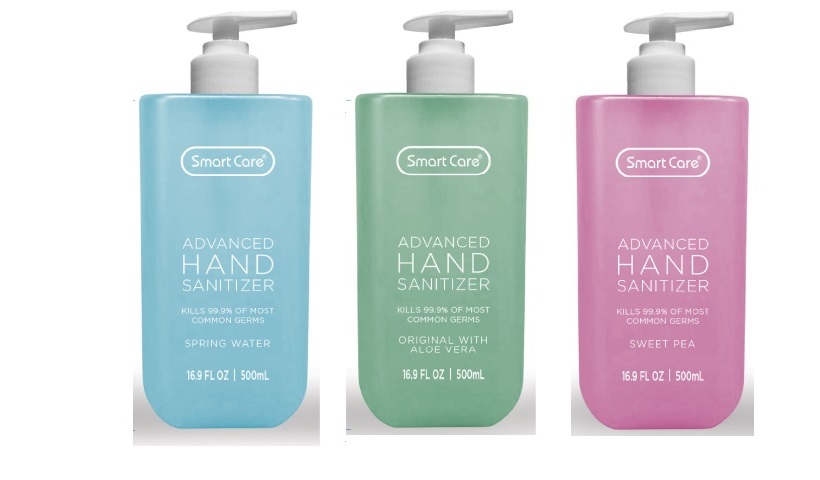 DRUG LABEL: Smart Care Advanced Hand Sanitizer
NDC: 54860-346 | Form: GEL
Manufacturer: Shenzhen Lantern Science Co., ltd.
Category: otc | Type: HUMAN OTC DRUG LABEL
Date: 20210125

ACTIVE INGREDIENTS: ALCOHOL 70 mL/100 mL
INACTIVE INGREDIENTS: WATER; ISOPROPYL ALCOHOL; GLYCERIN; CARBOMER HOMOPOLYMER, UNSPECIFIED TYPE; AMINOMETHYLPROPANOL; PROPYLENE GLYCOL; ISOPROPYL MYRISTATE; ALOE VERA LEAF; .ALPHA.-TOCOPHEROL ACETATE

Smart Care® ADVANCED HAND SANITIZER

Active Ingredients

Ethyl Alcohol 70% v/v

Purpose

Antiseptic

Use:

To help reduce bacteria and germs on the skin

Warnings:

For external use only: hands

Flammable, keep away from fire or flame

When using this product • Keep out of eyes • In case of contact with eyes, flush thoroughly with water • Avoid contact with broken skin • Do not inhale or ingest

Keep out of reach of children

If swallowed, get medical help or contact a Poison Control Center right away

Directions:

Put a thumbnail size amount in your palm and rub your hands together briskly until dry. Children under 6 years of age should be supervised when using this product. Not recommended for infants.

Other Information:

• Do not store above 100°F(38°C) • May discolor some fabrics • Harmful to wood finishes and plastics

Inactive Ingredients:

Water(Aqua),Isopropyl Alcohol, Glycerin, Carbomer, Aminomethyl Propanol, Fragrance, Propylene Glycol, Isopropyl Myristate, Aloe Barbadensis Leaf Juice, Tocopheryl Acetate

KILLS 99.9% OF MOST COMMON GERMS

SPRING WATER

ORIGINAL WITH ALOE VERA

SWEET PEA

SMARTCAREUS.COM

QUESTIONS OR COMMENTS?

1-877-274-8358 TOLL FREE IN U.S.A.

1-909-434-0911 INTERNATIONAL

PATENTS, COPYRIGHTS & TRADEMARKS GRANTED OR PENDING WORLDWIDE

DISTRIBUTED BY ASHTEL STUDIOS INC.

ONTARIO, CALIFORNIA 91761

DESIGNED IN U.S.A. • MADE IN CHINA